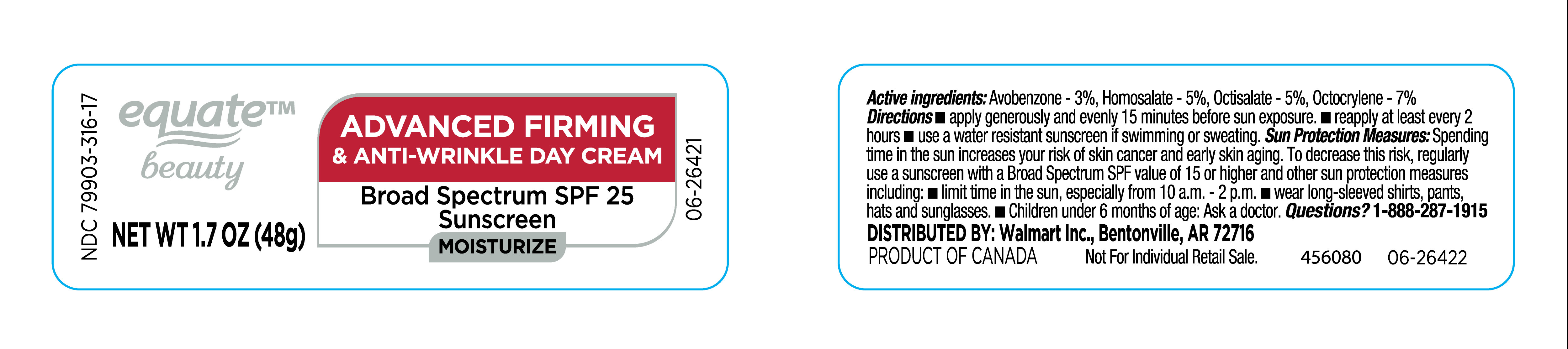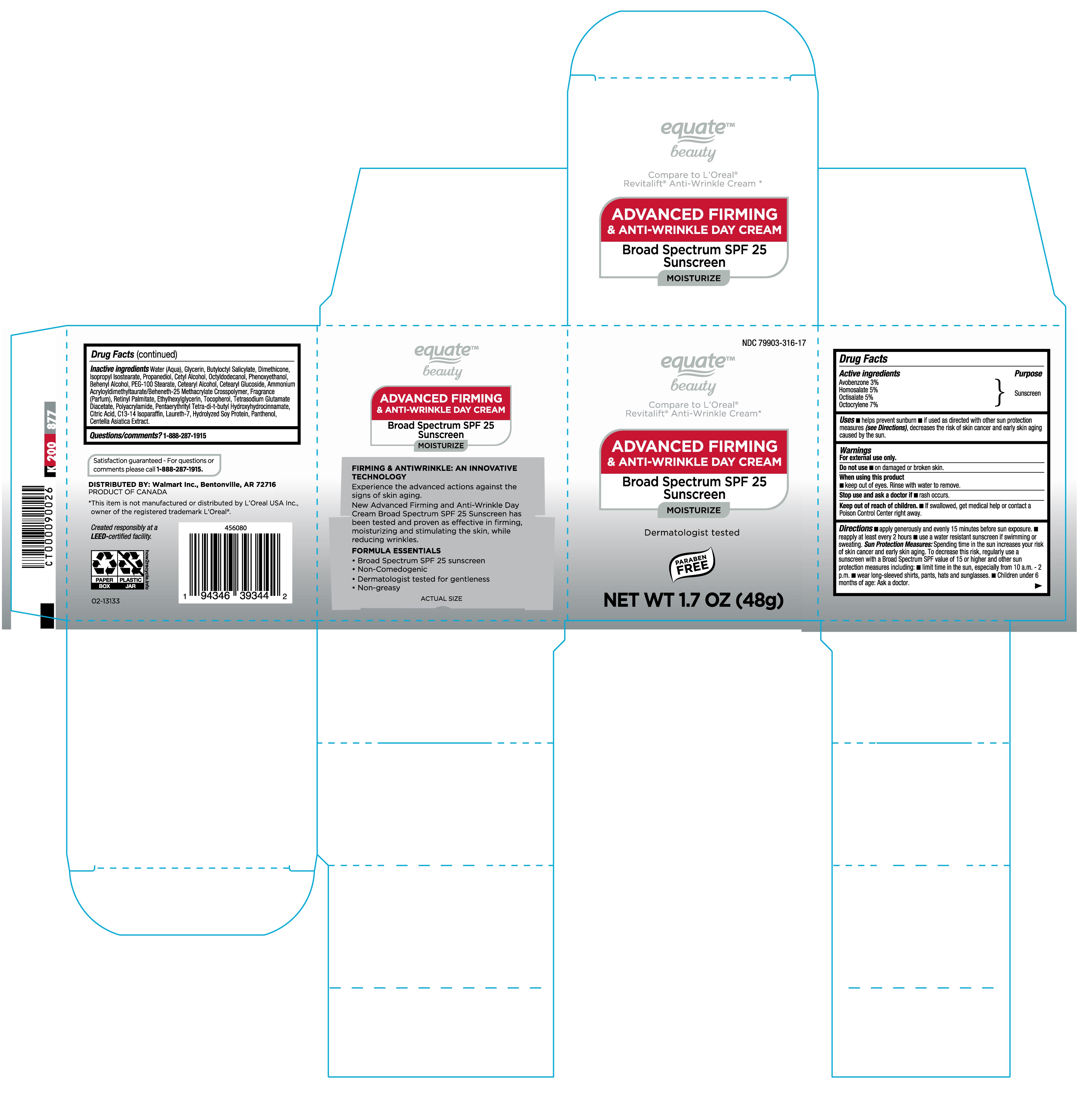 DRUG LABEL: Equate
NDC: 79903-316 | Form: CREAM
Manufacturer: WALMART INC
Category: otc | Type: HUMAN OTC DRUG LABEL
Date: 20250414

ACTIVE INGREDIENTS: OCTOCRYLENE 70 mg/1 g; HOMOSALATE 50 mg/1 g; AVOBENZONE 30 mg/1 g; OCTISALATE 50 mg/1 g
INACTIVE INGREDIENTS: OCTYLDODECANOL; AMMONIUM ACRYLOYLDIMETHYLTAURATE/BEHENETH-25 METHACRYLATE CROSSPOLYMER (52000 MPA.S); ISOPROPYL ISOSTEARATE; DIMETHICONE; TETRASODIUM GLUTAMATE DIACETATE; PROPANEDIOL; PHENOXYETHANOL; GLYCERIN; FRAGRANCE CLEAN ORC0600327; CITRIC ACID; HYDROLYZED SOY PROTEIN (ENZYMATIC; 2000 MW); BUTYLOCTYL SALICYLATE; CETYL ALCOHOL; PEG-100 STEARATE; POLYACRYLAMIDE (10000 MW); WATER; BEHENYL ALCOHOL; CETEARYL GLUCOSIDE; CETEARYL ALCOHOL; RETINYL PALMITATE; ETHYLHEXYLGLYCERIN; TOCOPHEROL; PANTHENOL; PENTAERYTHRITYL TETRA-DI-T-BUTYL HYDROXYHYDROCINNAMATE; C13-14 ISOPARAFFIN; LAURETH-7; CENTELLA ASIATICA TRITERPENOIDS

NDC-79903-316-17, Advanced Firming & Anti Wrinkle Day Cream

Active Ingredients

Avobenzone 3%

Homosalate 5%

Octisalate 5%

Octocrylene 7%

Purpose

Sunscreen

Uses

- Helps prevent sunburn
- If used as directed with other sun protection measures (see Directions), decreases the risk of skin cancer and early skin aging caused by the sun.

Warnings

For External use only.

Do not use

- On damaged or broken skin.

When using this product

- Keep out of eyes. Rinse with water to remove.

Stop use and ask a doctor if

- rash occurs.

Keep out of reach of children

- If swallowed, get medical help or contact a Poison Control Center right away.

Directions

- Apply generously and evenly 15 minutes before sun exposure.
- reapply at least every 2 hours.
- use a water resistant sunscreen if swimming or sweating.

Sun Protection Measures: Spending time in the sun increases your risk of skin cancer and early skin aging. To decrease this risk, regularly use a sunscreen with a Broad Sopectrum SPF value of 15 or higher and other sun protection measures including:

- Limit time in the sun, especially from 10 am-2 pm.
- Wear long sleeved shirts, pants, hats and sunglasses.
- Children under 6 months of age: Ask a doctor.

Inactive Ingredients

Water (Aqua), Glycerin, Butyloctyl Salicylate, Dimethicone, Isopropyl Isostearate, Propanediol, Cetyl Alcohol, Octyldodecanol, Phenoxyethanol, Bahenyl Alcohol, PEG-100 Stearate, Cetearyl Alcohol, Cetearyl Glucoside, Ammonium Acryloyldimethyltaurate/Beheneth-25 Methacrylate Crosspolymer, Fragrance (Parfum), Retinyl Palmitate, Ethylhexylglycerin, Tocopherol, Tetrasodium Glutamate Diacetate, Polyacrylamide, Pentaerythrityl Tetra-di-t-butyl Hydroxyhydrocinnamate, Citric Acid, C13-14 Isoparaffin, Laureth-7, Hydrolyzed Soy Protein, Panthenol, Centella Asiatica Extract.

Questions/comments?

1-888-287-1915